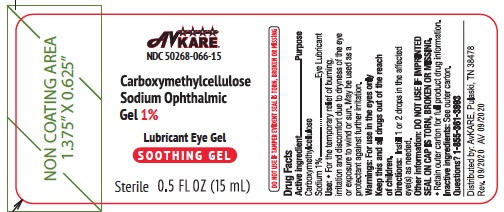 DRUG LABEL: carboxymethylcellulose sodium
NDC: 50268-066 | Form: GEL
Manufacturer: AvPAK
Category: otc | Type: HUMAN OTC DRUG LABEL
Date: 20240306

ACTIVE INGREDIENTS: CARBOXYMETHYLCELLULOSE SODIUM 10 mg/1 mL
INACTIVE INGREDIENTS: BORIC ACID; CALCIUM CHLORIDE; MAGNESIUM CHLORIDE; POTASSIUM CHLORIDE; WATER; SODIUM BORATE; SODIUM CHLORIDE

Carboxymethylcellulose Sodium Ophthalmic Gel 1%
Lubricant Eye Gel

Drug Facts

Active ingredient

Carboxymethylcellulose sodium 1%

Purpose

Eye lubricant

Uses

- For the temporary relief of burning, irritation, and discomfort due to dryness of the eye or exposure to wind or sun.
- May be used as a protectant against further irritation.

Warnings

- For use in the eyes only.
- To avoid contamination, do not touch tip of container to any surface. Replace cap after using.
- If solution changes color or becomes cloudy, do not use.

Stop use and ask a doctor if you experience eye pain, changes in vision, continued redness or irritation of the eye, or if the condition worsens or persists for more than 72 hours.

KEEP OUT OF REACH OF CHILDREN

Keep this and all drugs out of the reach of children. If swallowed, get medical help or contact a Poison Control Center right away (1-800-222-1222).

Directions

Shake well before use.

Instill 1 or 2 drops in the affected eye(s) as needed.

Other information

- Do Not Use if imprinted seal on cap is torn, broken or missing.
- Discard 90 days after opening.
- Store at room temperature 15°-30°C (59°-86°F).
- Retain outer carton for full product drug information.

Inactive ingredients

Boric acid, calcium chloride, magnesium chloride, potassium chloride, purified water, sodium borate, sodium chloride. Stabilized Oxychloro Complex 2.5%. May contain hydrochloric acid and/or sodium hydroxide to adjust pH.

Questions or comments?

1-855-361-3993

Distributed by:
AvKARE

Pulaski, TN 38478

Rev. 09/2020 AV 09/2020